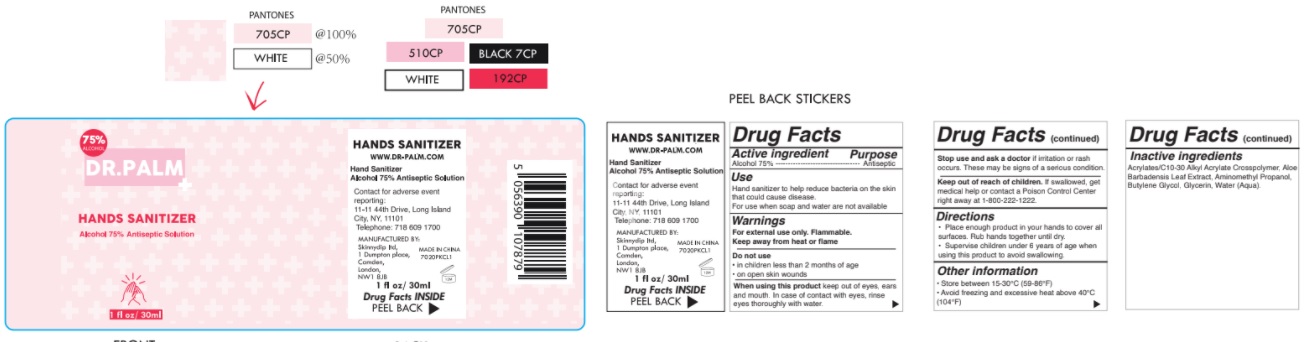 DRUG LABEL: Dr. Palm Hand sanitizer
NDC: 81236-001 | Form: GEL
Manufacturer: SKINNYDIP LIMITED
Category: otc | Type: HUMAN OTC DRUG LABEL
Date: 20210419

ACTIVE INGREDIENTS: ALCOHOL 75 mL/100 mL
INACTIVE INGREDIENTS: WATER; GLYCERIN; ALOE VERA LEAF; BUTYLENE GLYCOL; CARBOMER INTERPOLYMER TYPE A (ALLYL SUCROSE CROSSLINKED); AMINOMETHYLPROPANOL

Dr. Palm

Active Ingredient

Alcohol 75%

Purpose

Antiseptic

Uses

- Hand sanitizer to help reduce bacteria on the skin that could cause disease.
- For use when soap and water are not available

warnings

For external use only. Flammable. Keep away from heat or flame.

- Stop use and ask a doctor if irritation or rash occurs. These may be signs of a serious condition.

Do not use

- in children less than 2 months of age.
- on open skin wounds.

When using this product

- keep out of eyes, ears and mouth. In case of contact with eyes, rinse eyes thoroughly with water.

Directions

- Place enough product in your hands to cover all surfaces.
- Rub hands together until dry.
- Supervise children under 6 years of age when using this product to avoid swallowing.

Keep out of reach of children.

- If swallowed, get medical help or contact a Poison Control Center right away at 1-800-222-1222.

Inactive Ingredients.

Acrylates/C10-30 Alkyl Acrylate Crosspolymer, Aloe Barbadensis Leaf Extract, Aminomethyl Propanol,Butylene Glycol, Glycerin, Water (Aqua).

Other information.

• Store between 15-30°C (59-86°F)
• Avoid freezing and excessive heat above 40°C(104°F)